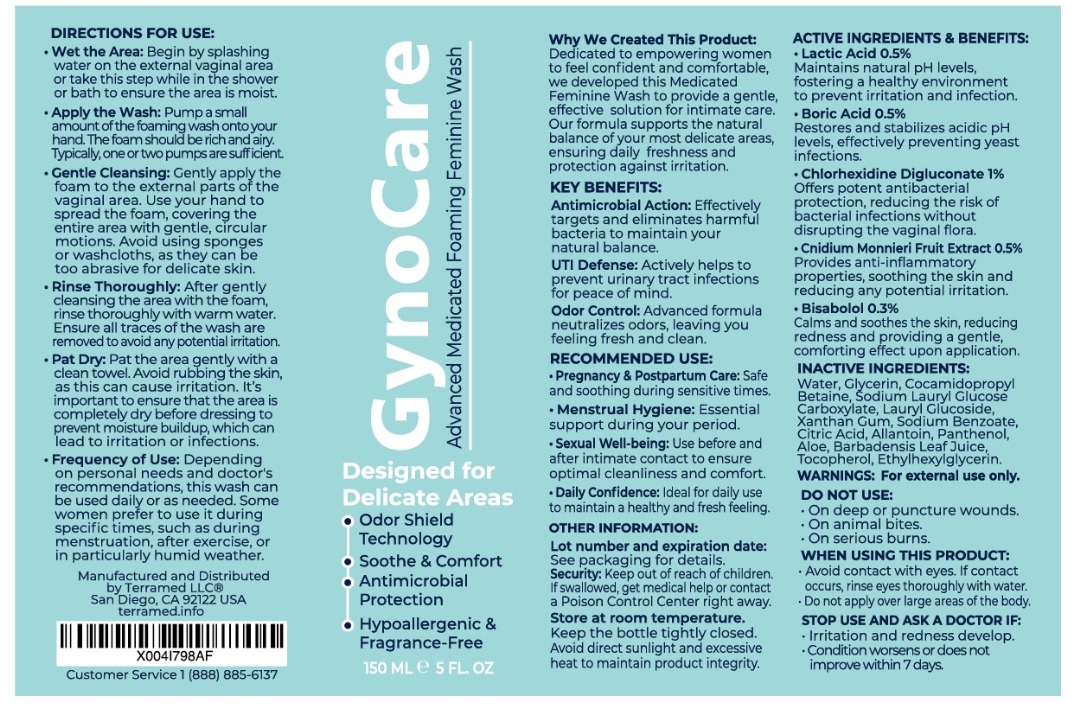 DRUG LABEL: Medicated Foaming Feminine
NDC: 83004-015 | Form: GEL
Manufacturer: Rida LLC
Category: homeopathic | Type: HUMAN OTC DRUG LABEL
Date: 20250306

ACTIVE INGREDIENTS: LACTIC ACID 0.5 g/100 mL; BORIC ACID 0.5 g/100 mL; CHLORHEXIDINE GLUCONATE 1 g/100 mL; CNIDIUM MONNIERI FRUIT OIL 0.5 g/100 mL; LEVOMENOL 0.3 g/100 mL
INACTIVE INGREDIENTS: WATER; COCAMIDOPROPYL BETAINE; SODIUM LAURYL GLYCOL CARBOXYLATE; LAURYL GLUCOSIDE; XANTHAN GUM; SODIUM BENZOATE; CITRIC ACID; ALLANTOIN; PANTHENOL; ALOE VERA LEAF; TOCOPHEROL; ETHYLHEXYLGLYCERIN; GLYCERIN

Active Ingredient Purpose

● Lactic Acid 0.5%: Maintains natural pH levels, fostering a healthy environment to prevent irritation and infections.

● Boric Acid 0.5%: Restores and stabilizes acidic pH levels, effectively preventing yeast infections.

● Chlorhexidine Digluconate 1%: Offers potent antibacterial protection, reducing the risk of bacterial infections without disrupting the vaginal flora.

● Cnidium Monnieri Fruit Extract 0.5%: Provides anti-inflammatory properties, soothing the skin and reducing any potential irritation.

● Bisabolol 0.3%: Calms and soothes the skin, reducing redness and providing a gentle, comforting effect upon application.

Uses

● Antimicrobial action: Effectively targets and eliminates harmful bacteria to maintain natural balance.
● UTI Defense: Actively helps to prevent urinary tract infections.
● Odor Control: Neutralizes odors, leaving you feeling fresh and clean.

Warnings

● For external use only.

● Do not use:
○ On broken or punctured wounds.
○ On animal bites.
○ On serious burns.

● When using this product:
○ Avoid contact with eyes. If contact occurs, rinse thoroughly with water.
○ Do not apply large amounts to the body.

● Stop use and ask a doctor if:
○ Irritation or redness develops.
○ Condition worsens or does not improve within 7 days.

Directions

● Wet the area: Begin by splashing water on the external vaginal area or take this step while in the shower or bath to ensure the area is moist.
● Apply the wash: Pump a small amount of the foam onto your hand. The foam should be rich and airy. Typically, two pumps are sufficient.
● Gentle Cleansing: Gently apply foam to the delicate areas. Use your hand to spread the foam, covering the entire area with gentle, circular motions. Avoid using sponges or washcloths, as they can be too abrasive.
● Rinse thoroughly: After cleansing, rinse thoroughly with warm water. Ensure all traces of the wash are removed to avoid irritation.
● Pat dry: Gently pat the area with a clean towel. Avoid rubbing, as this may cause irritation. It's important to ensure the area is completely dry before dressing to prevent moisture buildup, which can lead to irritation or infections.

Other Information

● Lot number and expiration date: See packaging for details.
● Keep out of reach of children. If swallowed, call a poison control center right away.
● Store at room temperature. Keep the bottle tightly closed. Avoid direct sunlight and excessive heat to maintain product integrity.

Inactive ingredients

Water (Aqua), Glycerin, Cocamidopropyl Betaine, Sodium Lauryl Glucose Carboxylate, Lauryl Glucoside, Xanthan Gum, Sodium Benzoate
Citric Acid, Allantoin, Panthenol, Aloe Barbadensis Leaf Juice, Tocopherol (Vitamin E), Ethylhexylglycerin